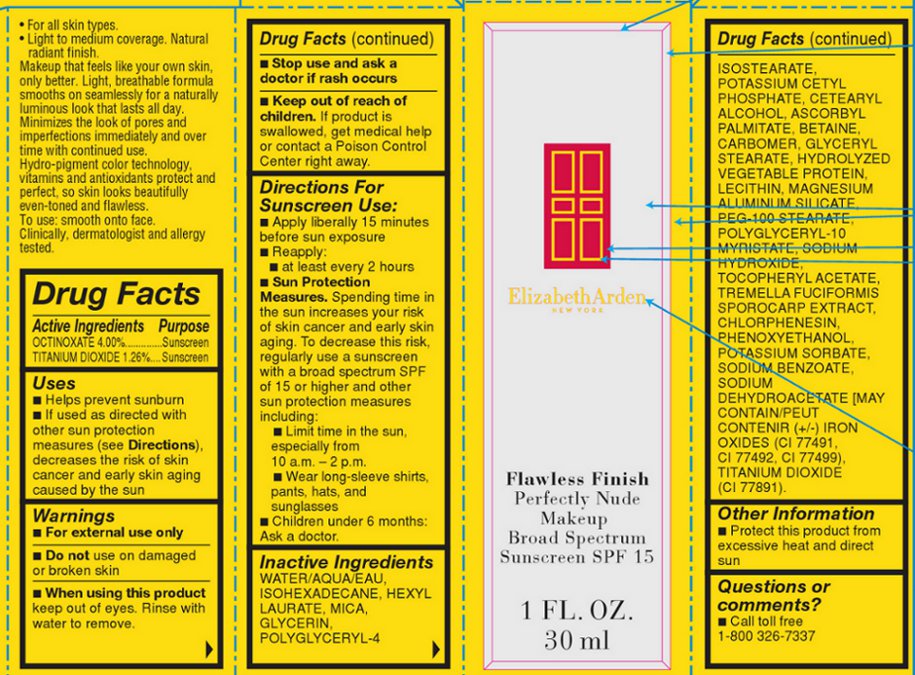 DRUG LABEL: FLAWLESS FINISH PERFECTLY NUDE MAKEUP BROAD SPECTRUM SUNSCREEN SPF 15 SHADE WARM MAHOGANY
NDC: 67938-2026 | Form: LOTION
Manufacturer: Elizabeth Arden, Inc
Category: otc | Type: HUMAN OTC DRUG LABEL
Date: 20130819

ACTIVE INGREDIENTS: OCTINOXATE 60 mg/1500 mg; TITANIUM DIOXIDE 18.9 mg/1500 mg
INACTIVE INGREDIENTS: WATER; ISOHEXADECANE; HEXYL LAURATE; MICA; GLYCERIN; POLYGLYCERYL-4 ISOSTEARATE; POTASSIUM CETYL PHOSPHATE; ASCORBYL PALMITATE; BETAINE; MAGNESIUM ALUMINUM SILICATE; PEG-100 STEARATE; SODIUM HYDROXIDE; CHLORPHENESIN; PHENOXYETHANOL; POTASSIUM SORBATE; SODIUM BENZOATE; SODIUM DEHYDROACETATE

250479

DESCRIPTION

Makeup that feels like your own skin, only better. Light, breathable formula smooths on seamlessly for a naturally luminous look that lasts all day. Minimizes the look of pores and imperfections immediately and over time with continued use. Hydro-pigment color technology, vitamins and antioxidants protect and perfect, so skin looks beautifully even-toned and flawless.

INDICATIONS & USAGE

smooth onto face.

WARNINGS

For external use only

OTC - ACTIVE INGREDIENT

OCTINOXATE 4.00%..............Sunscreen

TITANIUM DIOXIDE 1.26%....Sunscreen

INACTIVE INGREDIENT

WATER/AQUA/EAU, ISOHEXADECANE, HEXYL LAURATE, MICA, GLYCERIN, POLYGLYCERYL-4 ISOSTEARATE, POTASSIUM CETYL PHOSPHATE, CETEARYL ALCOHOL, ASCORBYL PALMITATE, BETAINE, CARBOMER, GLYCERYL STEARATE, HYDROLYZED VEGETABLE PROTEIN, LECITHIN, MAGNESIUM ALUMINUM SILICATE, PEG-100 STEARATE, POLYGLYCERYL-10 MYRISTATE, SODIUM HYDROXIDE, TOCOPHERYL ACETATE, TREMELLA FUCIFORMIS SPOROCARP EXTRACT, CHLORPHENESIN, PHENOXYETHANOL, POTASSIUM SORBATE, SODIUM BENZOATE, SODIUM DEHYDROACETATE [MAY CONTAIN/PEUT CONTENIR (+/-) IRON OXIDES (CI 77491, CI 77492, CI 77499), TITANIUM DIOXIDE (CI 77891).

OTC - DO NOT USE

Do not

use on damaged or broken skin

OTC - KEEP OUT OF REACH OF CHILDREN

Keep out of reach of children.

OTC - PURPOSE

Provides SPF 15 sun protection.

OTC - STOP USE

Stop use and ask a doctor if rash occurs

OTC - WHEN USING

keep out of eyes. Rinse with water to remove.